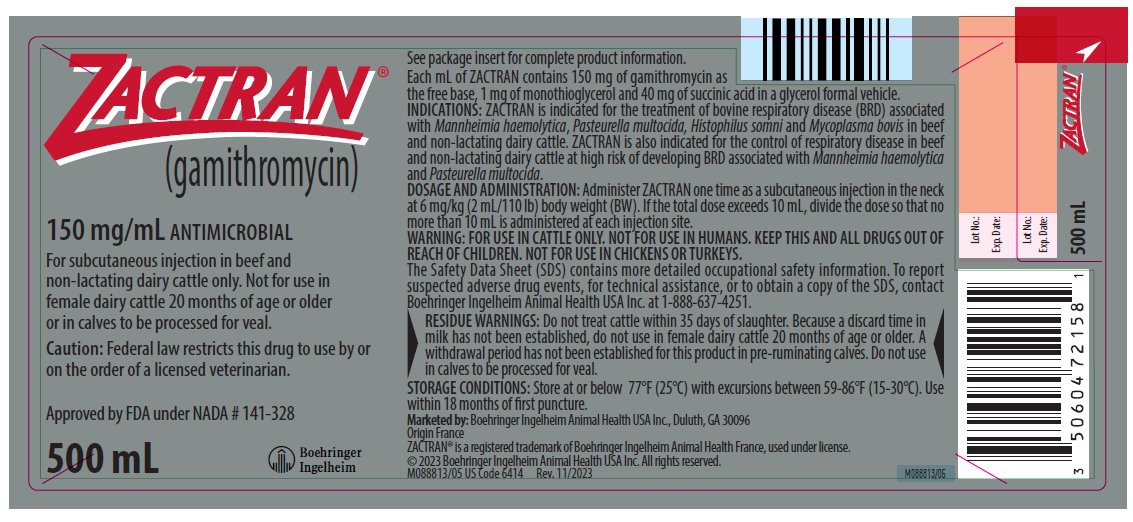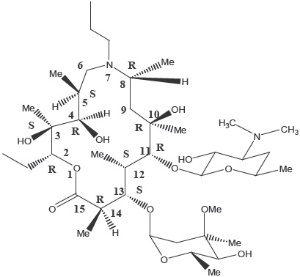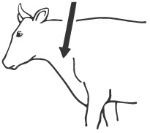 DRUG LABEL: ZACTRAN
NDC: 0010-7215 | Form: INJECTION, SOLUTION
Manufacturer: Boehringer Ingelheim Animal Health USA Inc.
Category: animal | Type: PRESCRIPTION ANIMAL DRUG LABEL
Date: 20241008

ACTIVE INGREDIENTS: gamithromycin 150 mg/1 mL
INACTIVE INGREDIENTS: monothioglycerol; succinic acid; glycerol formal

ZACTRAN®
(gamithromycin)

150 mg/mL ANTIMICROBIAL

For subcutaneous injection in beef and non-lactating dairy cattle only. Not for use in female dairy cattle 20 months of age or older or in calves to be processed for veal.

Caution: Federal law restricts this drug to use by or on the order of a licensed veterinarian.

READ ENTIRE BROCHURE CAREFULLY BEFORE USING THIS PRODUCT.

DESCRIPTION

ZACTRAN® Injection for Cattle is a ready to use sterile parenteral solution containing gamithromycin, a macrolide sub-class, 7a-azalide antimicrobial. Each mL of ZACTRAN contains 150 mg of gamithromycin as the free base, 1 mg of monothioglycerol and 40 mg of succinic acid in a glycerol formal vehicle.

The chemical name of gamithromycin is 1-Oxa-7-azacyclopentadecan-15-one,13-[(2,6-dideoy-3-C-methyl-3-O-methyl-alpha-L-ribo-hexopyranosyl)oxy]-2-ethyl-3,4,10-trihydroxy 3,5,8,10,12,14-hexamethyl-7-propyl-11-{[3,4,6-trideoxy-3-(dimethylamino)-beta-D-xylo-hexopyranosyl]oxy}-, [(2R*,3S*,4R*,5S*,8R*,10R*, 11R*,12S*,13S*,14R*)]-and the structure is shown below.

INDICATIONS

ZACTRAN is indicated for the treatment of bovine respiratory disease (BRD) associated with Mannheimia haemolytica, Pasteurella multocida, Histophilus somni and Mycoplasma bovis in beef and non-lactating dairy cattle. ZACTRAN is also indicated for the control of respiratory disease in beef and non-lactating dairy cattle at high risk of developing BRD associated with Mannheimia haemolytica and Pasteurella multocida.

DOSAGE and ADMINISTRATION

Administer ZACTRAN one time as a subcutaneous injection in the neck at 6 mg/kg (2 mL/110 lb) body weight (BW). If the total dose exceeds 10 mL, divide the dose so that no more than 10 mL is administered at each injection site.

Body Weight (lb) | Dose Volume (mL)
110 | 2
220 | 4
330 | 6
440 | 8
550 | 10
660 | 12
770 | 14
880 | 16
990 | 18
1100 | 20

Animals should be appropriately restrained to achieve the proper route of administration. Use sterile equipment. Inject under the skin in front of the shoulder (see illustration).

CONTRAINDICATIONS

As with all drugs, the use of ZACTRAN is contraindicated in animals previously found to be hypersensitive to this drug.

WARNING:

FOR USE IN CATTLE ONLY.

NOT FOR USE IN HUMANS.

KEEP THIS AND ALL DRUGS OUT OF REACH OF CHILDREN.

NOT FOR USE IN CHICKENS OR TURKEYS.

The Safety Data Sheet (SDS) contains more detailed occupational safety information. To report suspected adverse drug events, for technical assistance, or to obtain a copy of the SDS, contact Boehringer Ingelheim Animal Health USA Inc. at 1-888-637-4251. For additional information about adverse drug experience reporting for animal drugs, contact FDA at 1-888-FDA-VETS, or online at www.fda.gov/reportanimalae.

RESIDUE WARNINGS:

Do not treat cattle within 35 days of slaughter. Because a discard time in milk has not been established, do not use in female dairy cattle 20 months of age or older. A withdrawal period has not been established for this product in pre-ruminating calves. Do not use in calves to be processed for veal.

PRECAUTIONS

The effects of ZACTRAN on bovine reproductive performance, pregnancy, and lactation have not been determined. Subcutaneous injection of ZACTRAN may cause a transient local tissue reaction in some cattle that may result in trim loss of edible tissues at slaughter.

ADVERSE REACTIONS

Transient animal discomfort and mild to moderate injection site swelling may be seen in cattle treated with ZACTRAN.

CLINICAL PHARMACOLOGY

The macrolide antimicrobials as a class are weak bases and as such concentrate in some cells (such as pulmonary leukocytes). Prolonged exposure of extracellular pulmonary pathogens to macrolides appears to reflect the slow release of drug from its intracellular reservoir to the site of action, the pulmonary epithelial lining fluid (ELF). It is the ELF that is relevant to the successful treatment and control of BRD. Gamithromycin is primarily bacteriostatic at therapeutic concentrations. However, in vitro bactericidal activity has been observed at concentrations of 10 μg/mL (Mueller-Hinton broth) and after exposure to the 6-hour and 24-hour plasma samples derived from cattle dosed at 6 mg gamithromycin/kg BW.

Macrolides typically exhibit substantially higher concentrations in the alveolar macrophages and ELF as compared to concentrations observed in plasma. Gamithromycin concentrations in the ELF and ELF cells exceed the concentrations observed in the plasma. Postmortem gamithromycin concentrations in ELF exceed the MIC90 of M. haemolytica, H. somni and P. multocida through at least 72 hours after drug administration. Because M. haemolytica, P. multocida and H. somni are extracellular pathogens, drug concentrations in the ELF are considered to be clinically relevant. The postmortem area under the concentration-time curve (AUC) observed in lysed ELF cells (e.g., alveolar macrophages) are at least 300-times greater than that in the plasma. Although published studies suggest that inflammation can increase the release of drug from macrophages and neutrophils, these high concentrations in the alveolar macrophages should not be considered indicative of the magnitude or duration of response to the pathogens for which this product is indicated.

ZACTRAN administered subcutaneously in the neck of cattle at a single dosage of 6 mg/kg BW is rapidly and completely absorbed, with peak concentrations generally occurring within 1 hour after administration. Based upon plasma and lung homogenate data, the terminal half-life (T½) of gamithromycin is approximately 3 days. In vitro plasma protein binding studies show that 26% of the gamithromycin binds to plasma protein, resulting in free drug available for rapid and extensive distribution into body tissues. The free drug is rapidly cleared from the systemic circulation with a clearance rate of 712 mL/hr/kg and a volume of distribution of 25 L/kg. Dose proportionality was established based on AUC over a range of 3 mg/kg BW to 9 mg/kg BW. Biliary excretion of the unchanged drug is the major route of elimination.

MICROBIOLOGY

The minimum inhibitory concentrations (MIC's) of gamithromycin were determined for BRD isolates obtained from calves enrolled in BRD treatment field studies in the U.S. in 2004 using methods recommended by the Clinical and Laboratory Standards Institute (M31-A2). Isolates were obtained from pre-treatment nasopharyngeal swabs from each enrolled calf and from calves removed from the study due to BRD. The results are shown below in Table 1.

Table 1: Gamithromycin minimum inhibitory concentration (MIC) values* of indicated pathogens isolated from BRD treatment field studies in the U.S.
Indicated Pathogens | Years of Isolation | No. of isolates | MIC50** (µg/mL) | MIC90** (µg/mL) | MIC range (µg/mL)
M. haemolytica | 2004 | 89 | 1 | 1 | 0.5 to >32
P. multocida | 2004 | 79 | 0.5 | 1 | 0.12 to >32
H. somni | 2004 | 32 | 0.5 | 0.5 | 0.25 to 1
*The correlation between in vitro susceptibility data and clinical effectiveness is unknown.
** The lowest MIC to encompass 50% and 90% of the most susceptible isolates, respectively.

EFFECTIVENESS

The effectiveness of ZACTRAN for the treatment of BRD associated with Mannheimia haemolytica, Pasteurella multocida and Histophilus somni was demonstrated in a field study conducted at four geographic locations in the United States. A total of 497 cattle exhibiting clinical signs of BRD were enrolled in the study. Cattle were administered ZACTRAN (6 mg/kg BW) or an equivalent volume of sterile saline as a subcutaneous injection once on Day 0. Cattle were observed daily for clinical signs of BRD and were evaluated for clinical success on Day 10. The percentage of successes in cattle treated with ZACTRAN (58%) was statistically significantly higher (p<0.05) than the percentage of successes in the cattle treated with saline (19%).

The effectiveness of ZACTRAN for the treatment of BRD associated with M. bovis was demonstrated independently at two U.S. study sites. A total of 502 cattle exhibiting clinical signs of BRD were enrolled in the studies. Cattle were administered ZACTRAN (6 mg/kg BW) or an equivalent volume of sterile saline as a subcutaneous injection once on Day 0. At each site, the percentage of successes in cattle treated with ZACTRAN on Day 10 was statistically significantly higher than the percentage of successes in the cattle treated with saline (74.4% vs. 24% [p <0.001], and 67.4% vs. 46.2% [p = 0.002]). In addition, in the group of calves treated with gamithromycin that were confirmed positive for M. bovis (pre-treatment nasopharyngeal swabs), there were more calves at each site (45 of 57 calves, and 5 of 6 calves) classified as successes than as failures.

The effectiveness of ZACTRAN for the control of respiratory disease in cattle at high risk of developing BRD associated with Mannheimia haemolytica and Pasteurella multocida was demonstrated in two independent studies conducted in the United States. A total of 467 crossbred beef cattle at high risk of developing BRD were enrolled in the study. ZACTRAN (6 mg/kg BW) or an equivalent volume of sterile saline was administered as a single subcutaneous injection within one day after arrival. Cattle were observed daily for clinical signs of BRD and were evaluated for clinical success on Day 10 post-treatment. In each of the two studies, the percentage of successes in the cattle treated with ZACTRAN (86% and 78%) was statistically significantly higher (p = 0.0019 and p = 0.0016) than the percentage of successes in the cattle treated with saline (36% and 58%).

ANIMAL SAFETY

In a target animal safety study in healthy, six-month old beef cattle, ZACTRAN was administered by subcutaneous injection at 6, 18, and 30 mg/kg bodyweight (1, 3, and 5 times the labeled dose) on Day 0, 5, and 10 (3 times the labeled administration frequency). Injection site discomfort (neck twisting, attempts to scratch or lick the injection site, and pawing at the ground) was observed in calves in the 18 mg/kg BW and 30 mg/kg BW groups at 10 minutes post-treatment following each injection. Mild to moderate injection site swelling and pathology changes consistent with inflammation were observed in the gamithromycin-treated groups. Other than injection site reactions, no clinically relevant treatment-related effects were observed.

STORAGE CONDITIONS

Store at or below 77°F (25°C) with excursions between 59-86°F (15-30°C). Use within 18 months of first puncture.

HOW SUPPLIED

ZACTRAN is available in three ready-to-use bottle sizes. The 100, 250 and 500 mL bottles contain sufficient solution that will treat 10, 25 and 50 head of 550 lb (250 kg) cattle respectively.

Approved by FDA under NADA#141-328

Marketed by:

Boehringer Ingelheim Animal Health USA Inc.

Duluth, GA 30096

ZACTRAN® is a registered trademark of Boehringer Ingelheim Animal Health France, used under license.
© 2023 Boehringer Ingelheim Animal Health USA Inc. All rights reserved.

M088812/05 US Code 6411 Rev. 11/2023